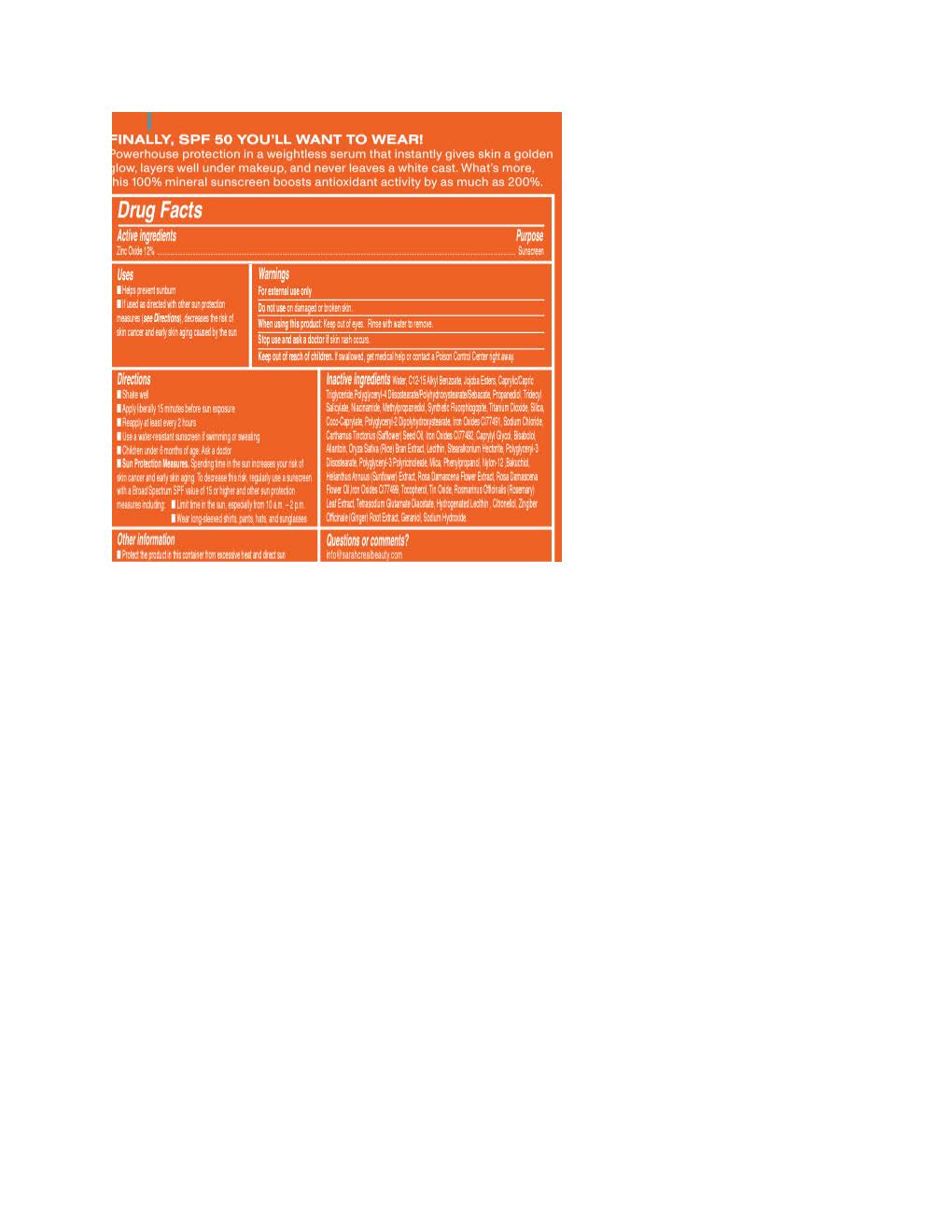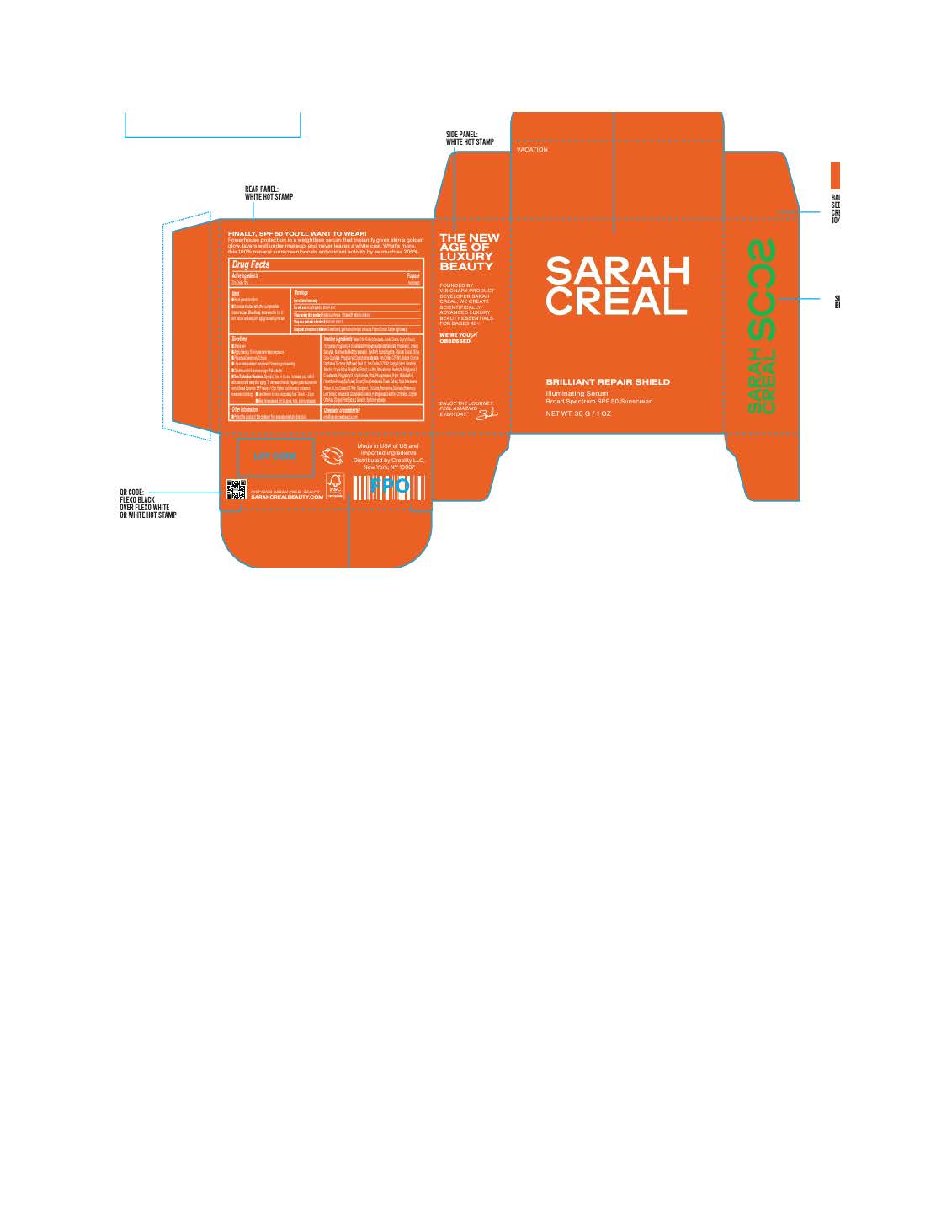 DRUG LABEL: Sarah Creal Brilliant Repair Shield
NDC: 83936-1230 | Form: LOTION
Manufacturer: Sarah Creal LLC
Category: otc | Type: HUMAN OTC DRUG LABEL
Date: 20251105

ACTIVE INGREDIENTS: ZINC OXIDE 12 g/100 g
INACTIVE INGREDIENTS: .ALPHA.-BISABOLOL, (+)-; POLYGLYCERYL-4 DIISOSTEARATE/POLYHYDROXYSTEARATE/SEBACATE; JOJOBA OIL; ORYZA SATIVA WHOLE; TRIDECYL SALICYLATE; SILICON DIOXIDE; TOCOPHEROL; CAPRYLYL GLYCOL; COCO-CAPRYLATE; NYLON-12; PHENYLPROPANOL; HELIANTHUS ANNUUS FLOWERING TOP; LECITHIN, SOYBEAN; METHYLPROPANEDIOL; POLYGLYCERYL-2 DIPOLYHYDROXYSTEARATE; ALLANTOIN; ALKYL (C12-15) BENZOATE; ROSMARINUS OFFICINALIS FLOWER; SODIUM HYDROXIDE; WATER; NIACINAMIDE; PROPANEDIOL; TETRASODIUM GLUTAMATE DIACETATE; SODIUM CHLORIDE; STEARALKONIUM HECTORITE; ROSMARINUS OFFICINALIS WHOLE; POLYGLYCERYL-3 DIISOSTEARATE; FERRIC OXIDE RED; FERRIC OXIDE YELLOW; BAKUCHIOL; .BETA.-CITRONELLOL, (S)-; TITANIUM DIOXIDE; CARTHAMUS TINCTORIUS FLOWER OIL; ZINGIBER OFFICINALE WHOLE; MICA; ROSA DAMASCENA FLOWER OIL

Sarah Creal Brilliant Repair Shield